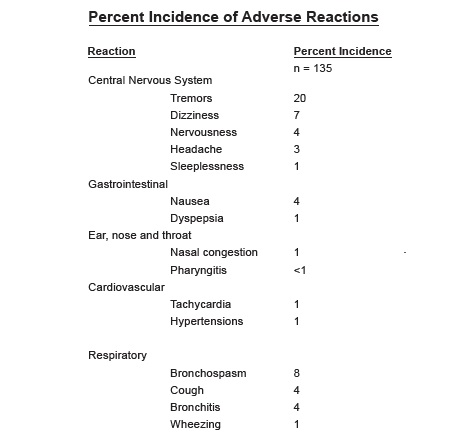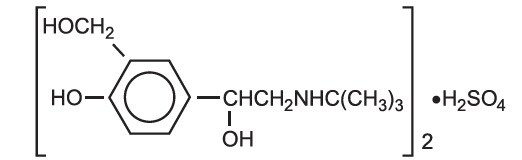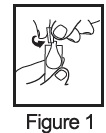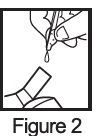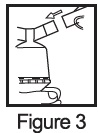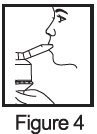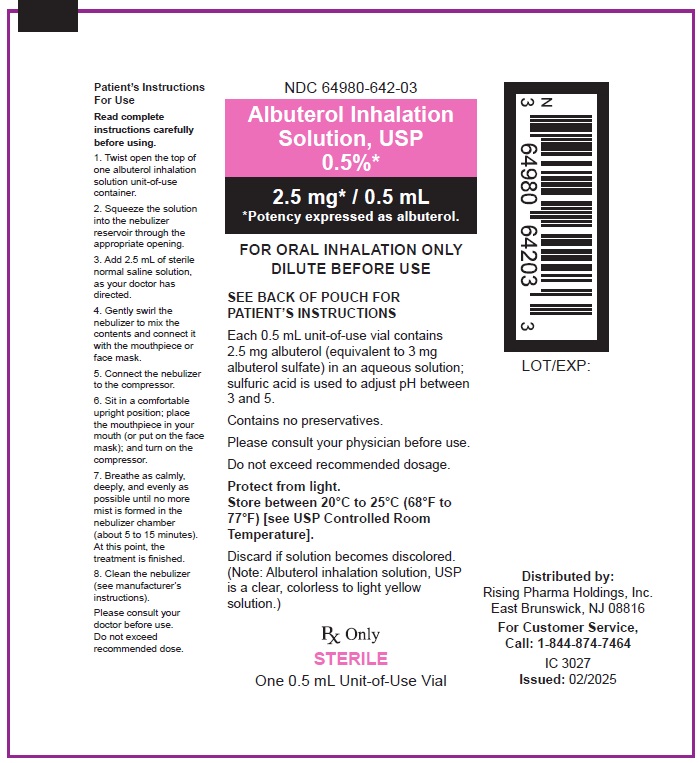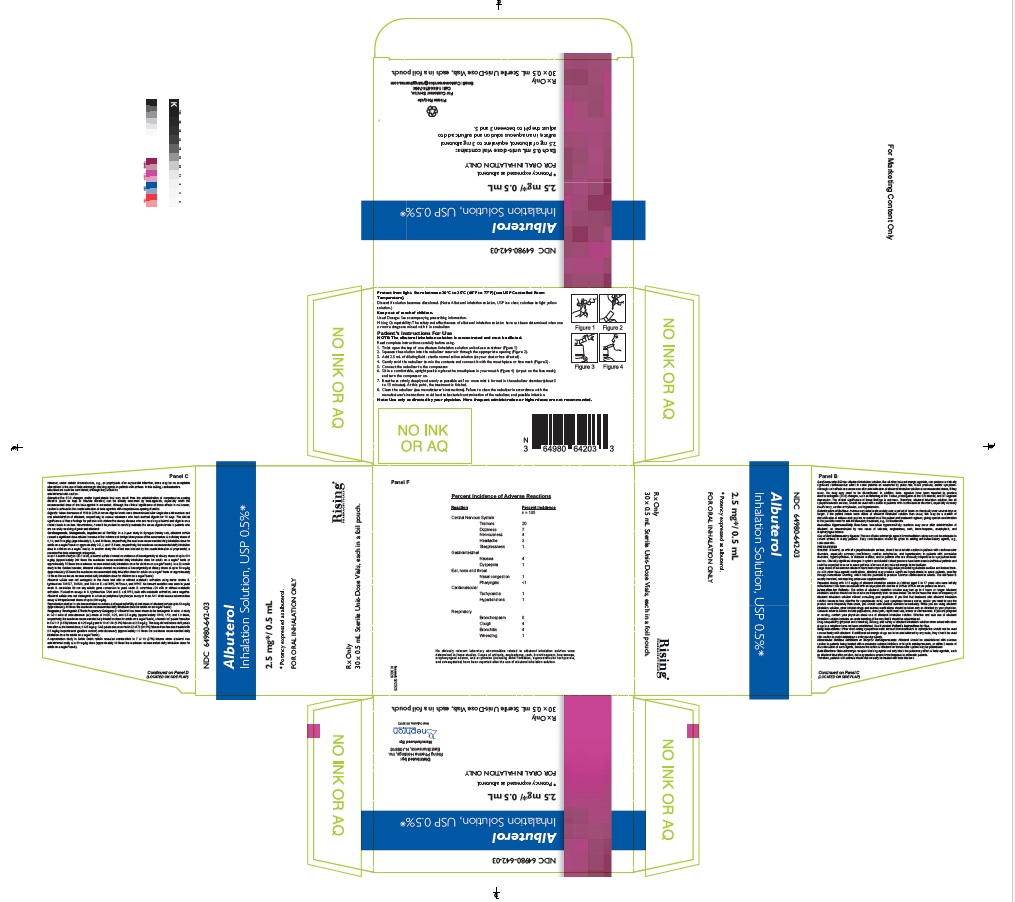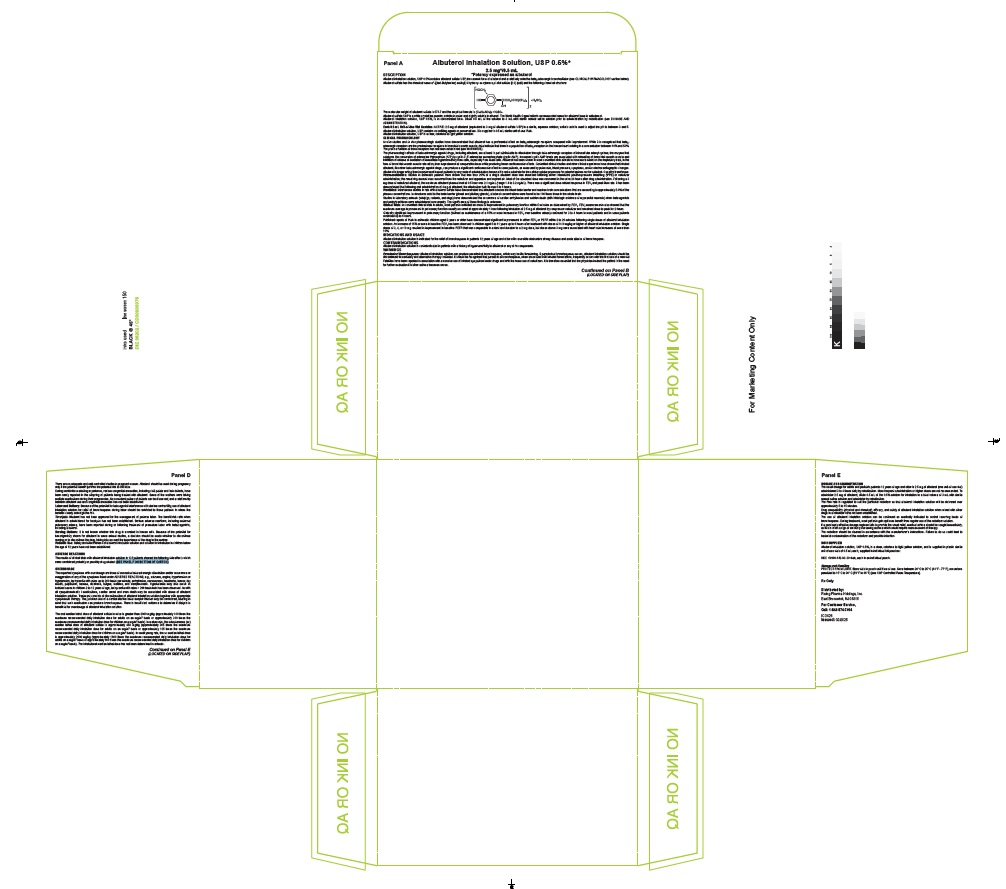 DRUG LABEL: Albuterol Sulfate
NDC: 64980-642 | Form: SOLUTION
Manufacturer: Rising Pharma Holdings, Inc.
Category: prescription | Type: HUMAN PRESCRIPTION DRUG LABEL
Date: 20250417

ACTIVE INGREDIENTS: ALBUTEROL SULFATE 2.5 mg/0.5 mL
INACTIVE INGREDIENTS: WATER; SULFURIC ACID

Albuterol Inhalation Solution, USP 0.5%*
2.5mg* / 0.5 mL

*Potency expressed as albuterol

DESCRIPTION

Albuterol inhalation solution, USP 0.5% contains albuterol sulfate USP, the racemic form of albuterol and a relatively selective beta2-adrenergic bronchodilator (see CLINICAL PHARMACOLOGYsection below). Albuterol sulfate has the chemical name α^1-[(tert-Butylamino) methyl]-4-hydroxy- m-xylene-α,α′-diol sulfate (2:1) (salt) and the following chemical structure:

The molecular weight of albuterol sulfate is 576.7 and the empirical formula is (C13H21NO3)2• H2SO4

Albuterol sulfate USP is a white crystalline powder, soluble in water and slightly soluble in ethanol. The World Health Organization’s recommended name for albuterol base is salbutamol.

Albuterol inhalation solution, USP 0.5%, is in concentrated form. Dilute 0.5 mL of the solution to 3 mL with sterile normal saline solution prior to administration by nebulization (see DOSAGE AND ADMINISTRATION).

Each 0.5 mL Unit-of-Use Vial Contains: ACTIVE: 2.5 mg of albuterol (equivalent to 3 mg of albuterol sulfate USP) in a sterile, aqueous solution; sulfuric acid is used to adjust the pH to between 3 and 5. Albuterol inhalation solution, USP contains no sulfiting agents or preservatives. It is supplied in 0.5 mL sterile unit-of-use Vials.

Albuterol inhalation solution, USP is a clear, colorless to light yellow solution.

CLINICAL PHARMACOLOGY

In vitro studies and in vivo pharmacologic studies have demonstrated that albuterol has a preferential effect on beta2-adrenergic receptors compared with isoproterenol. While it is recognized that beta2-adrenergic receptors are the predominant receptors in bronchial smooth muscle, data indicate that there is a population of beta2-receptors in the human heart existing in a concentration between 10% and 50%. The precise function of these receptors has not been established (see WARNINGS).

The pharmacologic effects of beta-adrenergic agonist drugs, including albuterol, are at least in part attributable to stimulation through beta-adrenergic receptors of intracellular adenyl cyclase, the enzyme that catalyzes the conversion of adenosine triphosphate (ATP) to cyclic-3’,5’-adenosine monophosphate (cyclic AMP). Increased cyclic AMP levels are associated with relaxation of bronchial smooth muscle and inhibition of release of mediators of immediate hypersensitivity from cells, especially from mast cells. Albuterol has been shown in most controlled clinical trials to have more effect on the respiratory tract, in the form of bronchial smooth muscle relaxation, than isoproterenol at comparable doses while producing fewer cardiovascular effects. Controlled clinical studies and other clinical experience have shown that inhaled albuterol, like other beta-adrenergic agonist drugs, can produce a significant cardiovascular effect in some patients, as measured by pulse rate, blood pressure, symptoms, and/or electrocardiographic changes. Albuterol is longer acting than isoproterenol in most patients by any route of administration because it is not a substrate for the cellular uptake processes for catecholamines nor for catechol- O-methyl transferase.

PHARMACOKINETICS

Pharmacokinetics: Studies in asthmatic patients have shown that less than 20% of a single albuterol dose was absorbed following either intermittent positive-pressure breathing (IPPB) or nebulizer administration; the remaining amount was recovered from the nebulizer and apparatus and expired air. Most of the absorbed dose was recovered in the urine 24 hours after drug administration. Following a 3 mg dose of nebulized albuterol, the maximum albuterol plasma level at 0.5 hour was 2.1 ng/mL (range 1.4 to 3.2 ng/mL). There was a significant dose-related response in FEV1and peak flow rate. It has been demonstrated that following oral administration of 4 mg of albuterol, the elimination half-life was 5 to 6 hours.

ANIMAL PHARMACOLOGY AND OR TOXICOLOGY

Preclinical:Intravenous studies in rats with albuterol sulfate have demonstrated that albuterol crosses the blood-brain barrier and reaches brain concentrations that are amounting to approximately 5.0% of the plasma concentrations. In structures outside the brain barrier (pineal and pituitary glands), albuterol concentrations were found to be 100 times those in the whole brain.

Studies in laboratory animals (minipigs, rodents, and dogs) have demonstrated the occurrence of cardiac arrhythmias and sudden death (with histologic evidence of myocardial necrosis) when beta-agonists and methylxanthines were administered concurrently. The significance of these findings is unknown.

CLINICAL STUDIES

Clinical Trials:In controlled clinical trials in adults, most patients exhibited an onset of improvement in pulmonary function within 5 minutes as determined by FEV1. FEV1measurements also showed that the maximum average improvement in pulmonary function usually occurred at approximately 1 hour following inhalation of 2.5 mg of albuterol by compressor-nebulizer and remained close to peak for 2 hours. Clinically significant improvement in pulmonary function (defined as maintenance of a 15% or more increase in FEV1over baseline values) continued for 3 to 4 hours in most patients and in some patients continued up to 6 hours.

Published reports of trials in asthmatic children aged 3 years or older have demonstrated significant improvement in either FEV1or PEFR within 2 to 20 minutes following single doses of albuterol inhalation solution. An increase of 15% or more in baseline FEV1has been observed in children aged 5 to 11 years up to 6 hours after treatment with doses of 0.10 mg/kg or higher of albuterol inhalation solution. Single doses of 3, 4, or 10 mg resulted in improvement in baseline PEFR that was comparable in extent and duration to a 2 mg dose, but doses above 3 mg were associated with heart rate increases of more than 10%.

INDICATIONS AND USAGE

Albuterol inhalation solution is indicated for the relief of bronchospasm in patients 12 years of age and older with reversible obstructive airway disease and acute attacks of bronchospasm.

CONTRAINDICATIONS

Albuterol inhalation solution is contraindicated in patients with a history of hypersensitivity to albuterol or any of its components.

WARNINGS

WARNINGS

Paradoxical Bronchospasm:Albuterol inhalation solution can produce paradoxical bronchospasm, which may be life threatening. If paradoxical bronchospasm occurs, albuterol inhalation solution should be discontinued immediately and alternative therapy instituted. It should be recognized that paradoxical bronchospasm, when associated with inhaled formulations, frequently occurs with the first use of a new vial.

Fatalities have been reported in association with excessive use of inhaled sympathomimetic drugs and with the home use of nebulizers. It is therefore essential that the physician instruct the patient in the need for further evaluation if his/her asthma becomes worse.

Cardiovascular Effects:Albuterol inhalation solution, like all other beta-adrenergic agonists, can produce a clinically significant cardiovascular effect in some patients as measured by pulse rate, blood pressure, and/or symptoms. Although such effects are uncommon after administration of albuterol inhalation solution at recommended doses, if they occur, the drug may need to be discontinued. In addition, beta-agonists have been reported to produce electrocardiogram (ECG) changes, such as flattening of the T wave, prolongation of the QTc interval, and ST segment depression. The clinical significance of these findings is unknown. Therefore, albuterol inhalation solution, like all sympathomimetic amines, should be used with caution in patients with cardiovascular disorders, especially coronary insufficiency, cardiac arrhythmias, and hypertension.

Deterioration of Asthma:Asthma may deteriorate acutely over a period of hours or chronically over several days or longer. If the patient needs more doses of albuterol inhalation solution than usual, this may be a marker of destabilization of asthma and requires re-evaluation of the patient and treatment regimen, giving special consideration to the possible need for anti-inflammatory treatment, e.g., corticosteroids.

Immediate Hypersensitivity Reactions:Immediate hypersensitivity reactions may occur after administration of albuterol, as demonstrated by rare cases of urticaria, angioedema, rash, bronchospasm, anaphylaxis, and oropharyngeal edema.

Use of Anti-Inflammatory Agents:The use of beta-adrenergic agonist bronchodilators alone may not be adequate to control asthma in many patients. Early consideration should be given to adding anti-inflammatory agents, e.g., corticosteroids.

PRECAUTIONS

GENERAL PRECAUTIONS

General:Albuterol, as with all sympathomimetic amines, should be used with caution in patients with cardiovascular disorders, especially coronary insufficiency, cardiac arrhythmias, and hypertension; in patients with convulsive disorders, hyperthyroidism, or diabetes mellitus; and in patients who are unusually responsive to sympathomimetic amines. Clinically significant changes in systolic and diastolic blood pressure have been seen in individual patients and could be expected to occur in some patients after use of any beta-adrenergic bronchodilator.

Large doses of intravenous albuterol have been reported to aggravate pre-existing diabetes mellitus and ketoacidosis. As with other beta-agonist medications, albuterol may produce significant hypokalemia in some patients, possibly through intracellular shunting, which has the potential to produce adverse cardiovascular effects. The decrease is usually transient, not requiring potassium supplementation.

Repeated dosing with 0.15 mg/kg of albuterol inhalation solution in children aged 5 to 17 years who were initially normokalemic has been associated with an asymptomatic decline of 20% to 25% in serum potassium levels.

PATIENT COUNSELING INFORMATION

Information for Patients: The action of albuterol inhalation solution may last up to 6 hours or longer. Albuterol inhalation solution should not be used more frequently than recommended. Do not increase the dose or frequency of albuterol inhalation solution without consulting your physician. If you find that treatment with albuterol inhalation solution becomes less effective for symptomatic relief, your symptoms become worse, and/or you need to use the product more frequently than usual, you should seek medical attention immediately. While you are using albuterol inhalation solution, other inhaled drugs and asthma medications should be taken only as directed by your physician. Common adverse effects include palpitations, chest pain, rapid heart rate, tremor or nervousness. If you are pregnant or nursing, contact your physician about use of albuterol inhalation solution. Effective and safe use of albuterol inhalation solution includes an understanding of the way that it should be administered.

Drug compatibility (physical and chemical), efficacy, and safety of albuterol inhalation solution when mixed with other drugs in a nebulizer have not been established. See illustrated Patient's Instructions for Use.

DRUG INTERACTIONS

Drug Interactions:Other short-acting sympathomimetic aerosol bronchodilators or epinephrine should not be used concomitantly with albuterol. If additional adrenergic drugs are to be administered by any route, they should be used with caution to avoid deleterious cardiovascular effects.

Monoamine Oxidase Inhibitors or Tricyclic Antidepressants:Albuterol should be administered with extreme caution to patients being treated with monoamine oxidase inhibitors or tricyclic antidepressants, or within 2 weeks of discontinuation of such agents, because the action of albuterol on the vascular system may be potentiated.

Beta-Blockers:Beta-adrenergic receptor blocking agents not only block the pulmonary effect of beta-agonists, such as albuterol inhalation solution, but may produce severe bronchospasm in asthmatic patients. Therefore, patients with asthma should not normally be treated with beta blockers. However, under certain circumstances, e.g., as prophylaxis after myocardial infarction, there may be no acceptable alternatives to the use of beta-adrenergic blocking agents in patients with asthma. In this setting, cardioselective beta blockers could be considered, although they should be administered with caution.

Diuretics:The ECG changes and/or hypokalemia that may result from the administration of nonpotassium-sparing diuretics (such as loop or thiazide diuretics) can be acutely worsened by beta-agonists, especially when the recommended dose of the beta-agonist is exceeded. Although the clinical significance of these effects is not known, caution is advised in the coadministration of beta-agonists with nonpotassium-sparing diuretics.

Digoxin:Mean decreases of 16% to 22% in serum digoxin levels were demonstrated after single-dose intravenous and oral administration of albuterol, respectively, to normal volunteers who had received digoxin for 10 days. The clinical significance of these findings for patients with obstructive airway disease who are receiving albuterol and digoxin on a chronic basis is unclear. Nevertheless, it would be prudent to carefully evaluate the serum digoxin levels in patients who are currently receiving digoxin and albuterol.

CARCINOGENESIS AND MUTAGENESIS AND IMPAIRMENT OF FERTILITY

Carcinogenesis, Mutagenesis, Impairment of Fertility:In a 2-year study in Sprague-Dawley rats, albuterol sulfate caused a significant dose-related increase in the incidence of benign leiomyomas of the mesovarium at e dietary doses of 2, 10, and 50 mg/kg (approximately 2, 8, and 40 times, respectively, the maximum recommended daily inhalation dose for adults on a mg/m^2basis or approximately 3/5, 3, and 15 times, respectively, the maximum recommended daily inhalation dose in children on a mg/m^2basis). In another study this effect was blocked by the coadministration of propranolol, a nonselective beta-adrenergic antagonist.

In an 18-month study in CD-1 mice, albuterol sulfate showed no evidence of tumorigenicity at dietary doses of up to 500 mg/kg (approximately 200 times the maximum recommended daily inhalation dose for adults on a mg/m^2basis or approximately 75 times the maximum recommended daily inhalation dose for children on a mg/m^2basis). In a 22-month study in the Golden hamster, albuterol sulfate showed no evidence of tumorigenicity at dietary doses of up to 50 mg/kg (approximately 25 times the maximum recommended daily inhalation dose for adults on a mg/m^2basis or approximately 10 times the maximum recommended daily inhalation dose for children on a mg/m^2basis).

Albuterol sulfate was not mutagenic in the Ames test with or without metabolic activation using tester strains S. typhimurium TA1537, TA1538, and TA98 or E. coliWP2, WP2uvrA, and WP67. No forward mutation was seen in yeast strain S. cerevisiaeS9 nor any mitotic gene conversion in yeast strain S. cerevisiae JD1 with or without metabolic activation. Fluctuation assays in S. typhimurium TA98 and E. coliWP2, both with metabolic activation, were negative. Albuterol sulfate was not clastogenic in a human peripheral lymphocyte assay or in an AH1 strain mouse micronucleus assay at intraperitoneal doses of up to 200 mg/kg.

Reproduction studies in rats demonstrated no evidence of impaired fertility at oral doses of albuterol sulfate up to 50 mg/kg (approximately 40 times the maximum recommended daily inhalation dose for adults on an mg/m^2basis).

Pregnancy

Teratogenic Effects

Pregnancy Teratogenic Effects Pregnancy Category C:Albuterol has been shown to be teratogenic in mice. A study in CD-1 mice at subcutaneous (sc) doses of 0.025, 0.25, and 2.5 mg/kg (approximately 1/100, 1/10, and 1.0 times, respectively, the maximum recommended daily inhalation dose for adults on a mg/m^2basis), showed cleft palate formation in 5 of 111 (4.5%) fetuses at 0.25 mg/kg and in 10 of 108 (9.3%) fetuses at 2.5 mg/kg. The drug did not induce cleft palate formation at the lowest dose, 0.025 mg/kg. Cleft palate also occurred in 22 of 72 (30.5%) fetuses from females treated with 2.5 mg/kg isoproterenol (positive control) subcutaneously (approximately 1.0 times the maximum recommended daily inhalation dose for adults on a mg/m^2basis).

A reproduction study in Stride Dutch rabbits revealed cranioschisis in 7 of 19 (37%) fetuses when albuterol was administered orally at a 50 mg/kg dose (approximately 80 times the maximum recommended daily inhalation dose for adults on a mg/m^2basis).

There are no adequate and well-controlled studies in pregnant women. Albuterol should be used during pregnancy only if the potential benefit justifies the potential risk to the fetus.

During worldwide marketing experience, various congenital anomalies, including cleft palate and limb defects, have been rarely reported in the offspring of patients being treated with albuterol. Some of the mothers were taking multiple medications during their pregnancies. No consistent pattern of defects can be discerned, and a relationship between albuterol use and congenital anomalies has not been established.

Labor and Delivery:Because of the potential for beta-agonist interference with uterine contractility, use of albuterol inhalation solution for relief of bronchospasm during labor should be restricted to those patients in whom the benefits clearly outweigh the risk.

Tocolysis:Albuterol has not been approved for the management of preterm labor. The benefit:risk ratio when albuterol is administered for tocolysis has not been established. Serious adverse reactions, including maternal pulmonary edema, have been reported during or following treatment of premature labor with beta 2-agonists, including albuterol.

NURSING MOTHERS

Nursing Mothers:It is not known whether this drug is excreted in human milk. Because of the potential for tumorigenicity shown for albuterol in some animal studies, a decision should be made whether to discontinue nursing or to discontinue the drug, taking into account the importance of the drug to the mother.

PEDIATRIC USE

Pediatric Use:Safety and effectiveness of albuterol inhalation solution and solution for inhalation in children below the age of 12 years have not been established.

ADVERSE REACTIONS

The results of clinical trials with albuterol inhalation solution in 135 patients showed the following side effects which were considered probably or possibly drug related:

No clinically relevant laboratory abnormalities related to albuterol inhalation solution were determined in these studies. Cases of urticaria, angioedema, rash, bronchospasm, hoarseness, oropharyngeal edema, and arrythmias (including atrial fibrillation, supraventricular tachycardia,
and extrasystoles) have been reported after the use of albuterol inhalation solution.

OVERDOSAGE

The expected symptoms with overdosage are those of excessive beta-adrenergic stimulation and/or occurrence or exaggeration of any of the symptoms listed under ADVERSE REACTIONS, e.g., seizures, angina, hypertension or hypotension, tachycardia with rates up to 200 beats per minute, arrhythmias, nervousness, headache, tremor, dry mouth, palpitation, nausea, dizziness, fatigue, malaise, and sleeplessness. Hypokalemia may also occur. In isolated cases in children 2 to 12 years of age, tachycardia with rates > 200 beats/min has been observed. As with all sympathomimetic l medications, cardiac arrest and even death may be associated with abuse of albuterol inhalation solution. Treatment consists of discontinuation of albuterol inhalation solution together with appropriate symptomatic therapy. The judicious use of a cardioselective beta-receptor blocker may be considered, bearing in mind that such medication can produce bronchospasm. There is insufficient evidence to determine if dialysis is beneficial for overdosage of albuterol inhalation solution.

The oral median lethal dose of albuterol sulfate in mice is greater than 2000 mg/kg (approximately 810 times the maximum recommended daily inhalation dose for adults on an mg/m^2basis or approximately 300 times the maximum recommended daily inhalation dose for children on a mg/m^2basis). In mature rats, the subcutaneous (sc) median lethal dose of albuterol sulfate is approximately 450 mg/kg (approximately 365 times the maximum recommended daily inhalation dose for adults on an mg/m^2basis or approximately 135 times the maximum recommended daily inhalation dose for children on a mg/m^2basis). In small young rats, the sc median lethal dose is approximately 2000 mg/kg (approximately 1600 times the maximum recommended daily inhalation dose for adults on a mg/m^2basis or approximately 600 times the maximum recommended daily inhalation dose for children on a mg/m^2basis). The inhalational median lethal dose has not been determined in animals.

DOSAGE AND ADMINISTRATION

The usual dosage for adults and pediatric patients 12 years of age and older is 2.5 mg of albuterol (one unit-of-use vial) administered 3 to 4 times daily by nebulization. More frequent administration or higher doses are not recommended. To administer 2.5 mg of albuterol, dilute 0.5 mL of the 0.5% solution for inhalation to a total volume of 3 mL with sterile normal saline solution and administer by nebulization.

The flow rate is regulated to suit the particular nebulizer so that albuterol inhalation solution will be delivered over approximately 5 to 15 minutes.

Drug compatibility (physical and chemical), efficacy, and safety of albuterol inhalation solution when mixed with other drugs in a nebulizer have not been established.

The use of albuterol inhalation solution can be continued as medically indicated to control recurring bouts of bronchospasm. During treatment, most patients gain optimum benefit from regular use of the nebulizer solution.

If a previously effective dosage regimen fails to provide the usual relief, medical advice should be sought immediately, as this is often a sign of seriously worsening asthma which would require reassessment of therapy.

The nebulizer should be cleaned in accordance with the manufacturer’s instructions. Failure to do so could lead to bacterial contamination of the nebulizer and possible infection.

HOW SUPPLIED

Albuterol inhalation solution, USP 0.5%, is a clear, colorless to light yellow solution, and is supplied in plastic sterile unit-of-use vials of 0.5 mL each, supplied in individual foil pouches:

NDC 64980-642-03: 30 vials, each in an individual pouch.

Storage and Handling

PROTECT FROM LIGHT. Store vials in pouch until time of use. Store between 20 °C to 25°C (68°F - 77°F), excursions permitted to 15 °C to 30 °C (59°F - 86°F) [see USP Controlled Room Temperature].

Rx Only

Distributed by:

Rising Pharma Holdings, Inc.

East Brunswick, NJ 08816

For Customer Service,

Call: 1-844-874-7464

IC 3028

Issued:02/2025

Manufactured By:
Nephron Pharmaceuticals Corporation
West Columbia, SC 29172

Patient Package Insert

Protect from light. Store between 20 °C to 25°C (68°F - 77°F) [see USP Controlled Room Temperature].

Discard if solution becomes discoloured (Note: Albuterol inhalation solution, USP is a clear, colorless to light yellow solution.)

Keep out of reach of children.

Usual Dosage: See accompanying prescribing information.

Mixing Compatibility: The safety and effectiveness of albuterol inhalation solution have not been determined when one or more drugs are mixed with it in a nebulizer.

NOTE: The albuterol inhalation solution is concentrated and must be diluted.

Read complete instructions carefully before using.

Patient's Instructions For Use

1. Twist open the top of one albuterol inhalation solution unit-of-use container (Figure 1).

2. Squeeze the solution into the nebulizer reservoir through the appropriate opening (Figure 2).

3. Add 2.5 mL of diluting fluid – sterile normal saline solution (as your doctor has directed).

4. Gently swirl the nebulizer to mix the contents and connect it with the mouthpiece or face mask (Figure 3).

5. Connect the nebulizer to the compressor.

6.Sit in a comfortable, upright position; place the mouthpiece in your mouth (Figure 4) (or put on the face mask); and turn the compressor on.

7. Breathe as calmly, deeply and evenly as possible until no more mist is formed in the nebulizer chamber (about 5 to 15 minutes). At this point, the treatment is finished.

8. Clean the nebulizer (see manufacturer’s instructions). Failure to clean the nebulizer in accordance with the manufacturer’s instructions could lead to bacterial contamination of the nebulizer, and possible infection.

Note: Use only as directed by your physician. More frequent administration or higher doses are not recommended.

PACKAGE LABEL.PRINCIPAL DISPLAY PANEL

Principal Display Panel – Pouch Label (individually wrapped vials)

NDC 64980-642-03

Principal Display Panel – Carton (30 individually wrapped vials)

NDC 64980-642-03